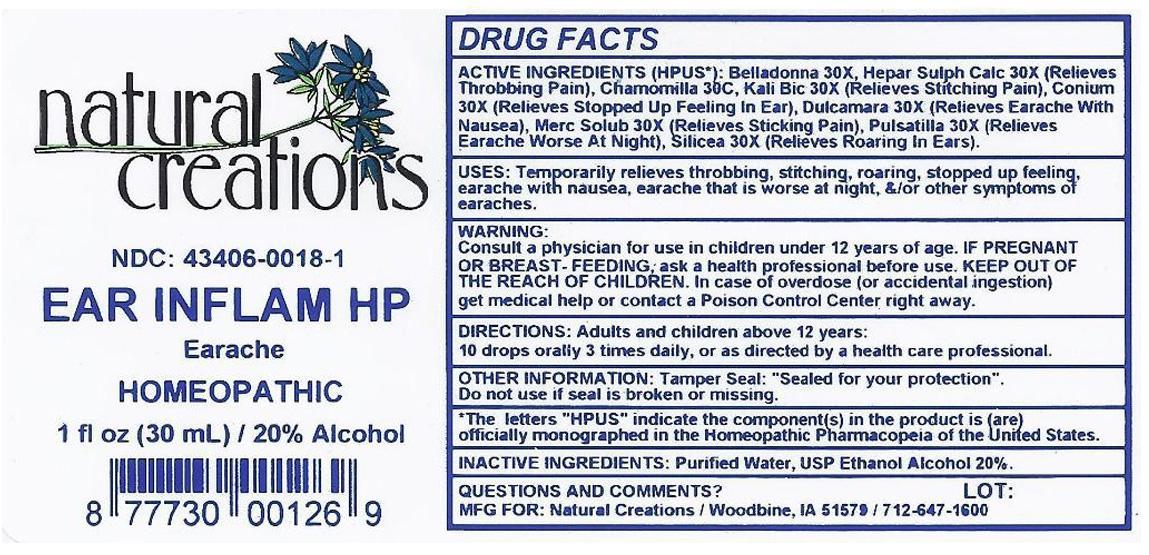 DRUG LABEL: EAR INFLAM HP
NDC: 43406-0018 | Form: LIQUID
Manufacturer: Natural Creations, Inc.
Category: homeopathic | Type: HUMAN OTC DRUG LABEL
Date: 20121031

ACTIVE INGREDIENTS: ATROPA BELLADONNA ROOT 30 [hp_X]/1 mL; CONIUM MACULATUM FLOWERING TOP 30 [hp_X]/1 mL; SOLANUM DULCAMARA TOP 30 [hp_X]/1 mL; CALCIUM SULFIDE 30 [hp_X]/1 mL; POTASSIUM DICHROMATE 30 [hp_X]/1 mL; MERCURIUS SOLUBILIS 30 [hp_X]/1 mL; PULSATILLA VULGARIS 30 [hp_X]/1 mL; SILICON DIOXIDE 30 [hp_X]/1 mL
INACTIVE INGREDIENTS: WATER; ALCOHOL

EAR INFLAM HP

ACTIVE INGREDIENT

ACTIVE INGREDIENTS (HPUS*): Belladonna 30X, Conium Maculatum 30X, Dulcamara 30X, Hepar Sulphuris Calcareum 30X, Kali Bichromicum 30X, Mercurius Solubilis 30X, Pulsatilla 30X, Silicea 30X

INDICATIONS AND USAGE

USES: Temporarily relieves throbbing, stitching, roaring, stopped up feeling, earache with nausea, earache that is worse at night, &/or other symptoms of earaches.

WARNING:

Consult a physician for use in children under 12 years of age. IF PREGNANT OR BREAST-FEEDING, ask a health care professional before use. KEEP OUT OF THE REACH OF CHILDREN. In case of overdose (or accidental ingestion) get medical help or contact a Poison Control Center right away.

DOSAGE AND ADMINISTRATION

DIRECTIONS: Adults and children above 12 years: 10 drops orally 3 times daily, or as directed by a health care professional.

OTHER INFORMATION: Tamper Seal: "Sealed for your protection."

Do not use if seal is broken or missing.

REFERENCES

*The letters "HPUS" indicate the components in the product are officially monographed in the Homeopathic Pharmacopeia of the United States.

INACTIVE INGREDIENTS: Purified Water, USP Ethanol Alcohol 20%

QUESTIONS AND COMMENTS?

MFG FOR: Natural Creations / Woodbine, IA / 51579 712.647.1600

LOT:

PURPOSE

USES: Temporarily relieves throbbing, stitching, roaring, stopped up feeling, earache with nausea, earache that is worse at night, &/or other symptoms of earaches.

KEEP OUT OF REACH OF CHILDREN

KEEP OUT OF THE REACH OF CHILDREN. In case of overdose (or accidental ingestion) get medical help or contact a Poison Control Center.

PACKAGE LABEL

NDC: 43406-0018-1

EAR INFLAM HP

Earache

HOMEOPATHIC

1 fl oz (30 mL) / 20% Alcohol

UPC: 877730001269